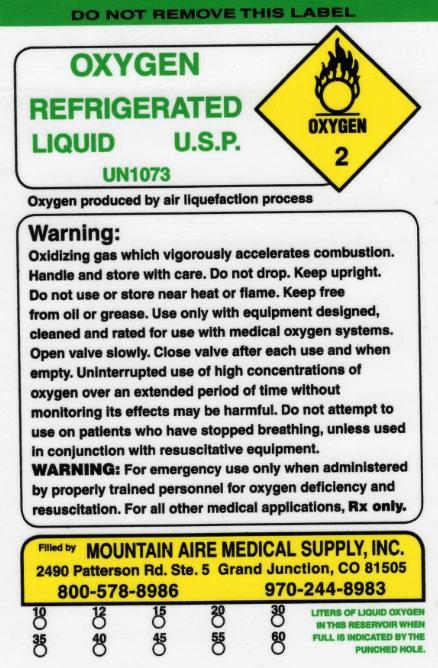 DRUG LABEL: OXYGEN
NDC: 62118-001 | Form: GAS
Manufacturer: Mountain Aire Medical Supply, Inc
Category: prescription | Type: HUMAN PRESCRIPTION DRUG LABEL
Date: 20221013

ACTIVE INGREDIENTS: OXYGEN 1 L/1 L

OXYGEN